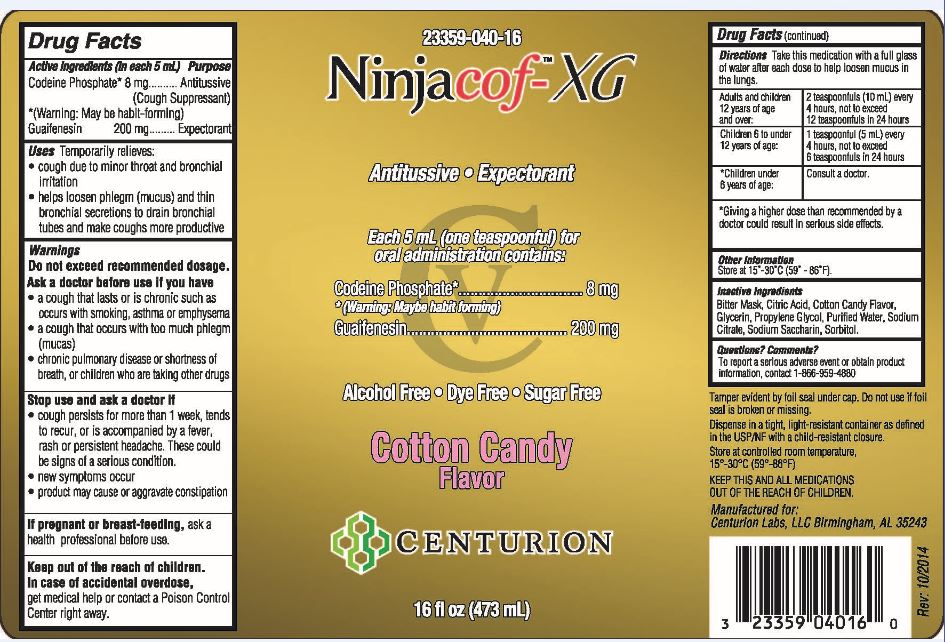 DRUG LABEL: Ninjacof-XG 
NDC: 23359-040 | Form: LIQUID
Manufacturer: Centurion Labs, LLC
Category: otc | Type: HUMAN OTC DRUG LABEL
Date: 20141120

ACTIVE INGREDIENTS: Codeine Phosphate 8 mg/5 mL; Guaifenesin 200 mg/5 mL
INACTIVE INGREDIENTS: Citric Acid Monohydrate; Glycerin; Propylene Glycol; Water; Sodium Citrate; Saccharin Sodium; Sorbitol

Ninjacof-XG

Active ingredients (in each 5 mL) | Purpose
Codeine Phosphate [Warning: May be habit forming] 8 mg | Antitussive (Cough Suppressant)
Guaifenesin 200 mg | Expectorant

INDICATIONS AND USAGE

Uses Temporarily relieves:

- cough due to minor throat and bronchial irritation
- helps loosen phlegm (mucus) and thin bronchial secretions to drain bronchial tubes and make coughs more productive

Warnings
Do not exceed recommended dosage.
Ask a doctor before use if you have

- a cough that lasts or is chronic such as occurs with smoking, asthma or emphysema
- a cough that occurs with too much phlegm (mucas)
- chronic pulmonary disease or shortness of breath, or children who are taking other drugs

Stop use and ask a doctor if

- cough persists for more than 1 week, tends to recur, or is accompanied by a fever, rash or persistent headache. These could be signs of a serious condition.
- new symptoms occur
- product may cause or aggravate constipation

If pregnant or breast-feeding, ask a
health professional before use.

KEEP OUT OF REACH OF CHILDREN

Keep out of the reach of children. In case of accidental overdose, get medical help or contact a Poison Control
Center right away.

INSTRUCTIONS FOR USE

Directions Take this medication with a full glass of water after each dose to help loosen mucus in the lungs

Adults and children 12 years of age and over: | 2 teaspoonfuls (10mL) every 4 hours, not to exceed 12 teasoonfuls in 24 hours
Children 6 to under 12 years of age: | 1 teaspoonful (5 mL) every 4 hours, not to exceed 6 teaspoonfuls in 24 hours
[Giving a higher dose than recommended by a doctor could result in serious side effects.] Children under 6 years of age: | Consult a doctor.

Other Information
Store at 15° - 30°C (59° - 86°F).

Inactive Ingredients

Bitter Mask, Citric Acid, Cotton Candy Flavor, Glycerin, Propylene Glycol, Purified Water, Sodium Citrate, Sodium Saccharin, Sorbitol.

Questions? Comments?
To report a serious adverse event or obtain product
information, contact 1-866-959-4880

PACKAGE LABEL.PRINCIPAL DISPLAY PANEL

23359-040-16

Ninjacof-XG

Cotton Candy
Flavor

CENTURION

16 fl oz (473 mL)

Tamper evident by foil seal under cap. Do not use if foil
seal is broken or missing.

Dispense in a tight, light-resistant container as defined
in the USP/NF with a child-resistant closure.

Store at controlled room temperature,
15°-30°C (59°-86°F)

KEEP THIS AND ALL MEDICATIONS
OUT OF THE REACH OF CHILDREN.

Manufactured for:
Centurion Labs, LLC Birmingham, AL 35243